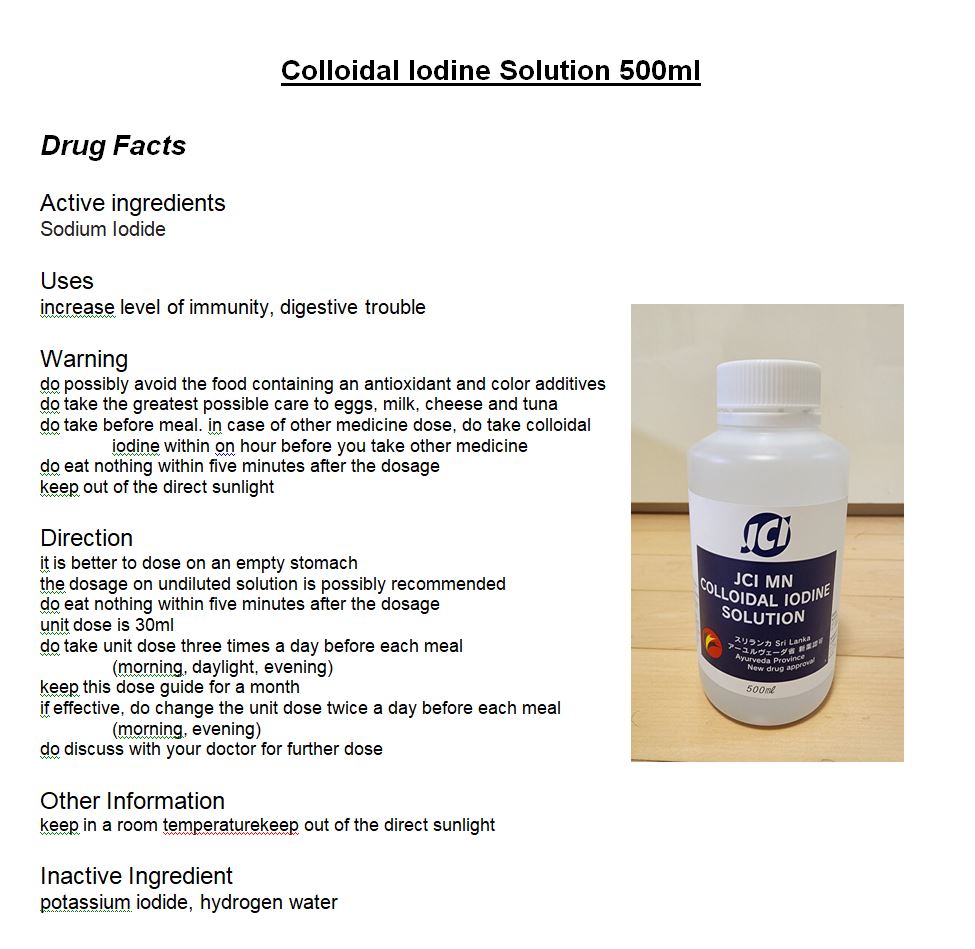 DRUG LABEL: Colloidal Iodine Solution
NDC: 69164-0003 | Form: SOLUTION
Manufacturer: JCI Colloidal Iodine Laboratory Co., Ltd.
Category: otc | Type: HUMAN OTC DRUG LABEL
Date: 20230523

ACTIVE INGREDIENTS: IODINE 2 g/100 mL
INACTIVE INGREDIENTS: WATER

Drug Facts

ACTIVE INGREDIENT

iodine

INACTIVE INGREDIENT

potassium iodide, hydrogen water

PURPOSE

increase level of immunity, digestive trouble

keep out of reach of the children

INDICATIONS AND USAGE

it is better to dose on an empty stomach

the dosage on undiluted solution is possibly recommended

do eat nothing within five minutes after the dosage

unit dose is 30ml

do take unit dose three times a day before each meal

(morning, daylight, evening)

keep this dose guide for a month

if effective, do change the unit dose twice a day before each meal

(morning, evening)

do discuss with your doctor for further dose

WARNINGS

do possibly avoid the food containing an antioxidant and color additives

do take the greatest possible care to eggs, milk, cheese and tuna

do take before meal. in case of other medicine dose, do take colloidal

iodine within on hour before you take other medicine

do eat nothing within five minutes after the dosage

keep out of the direct sunlight

DOSAGE AND ADMINISTRATION

for oral use only